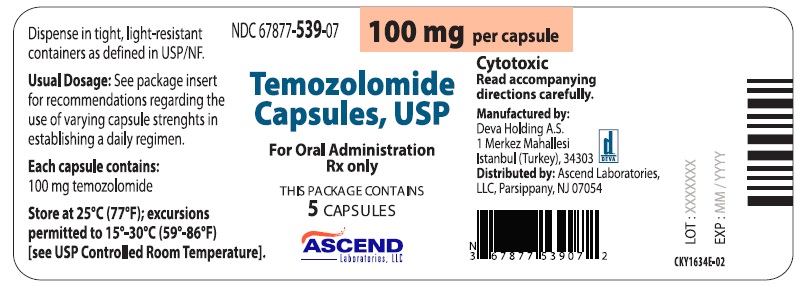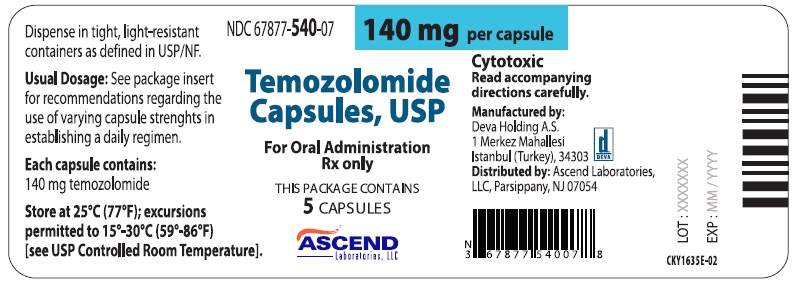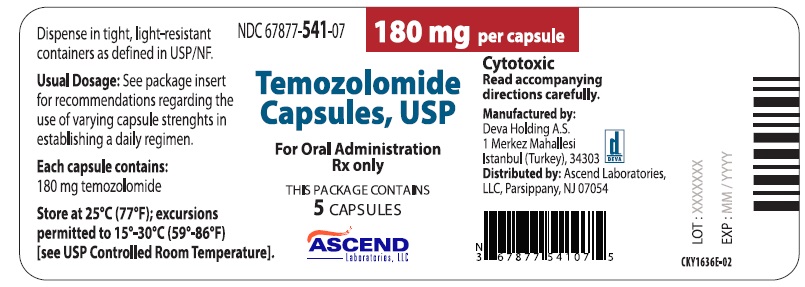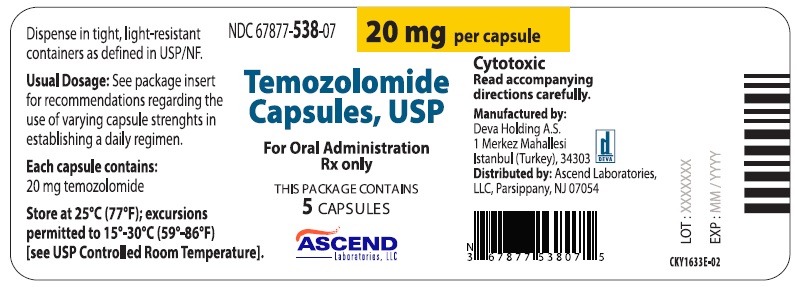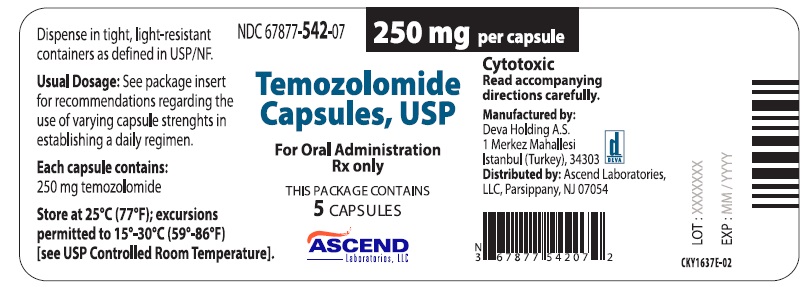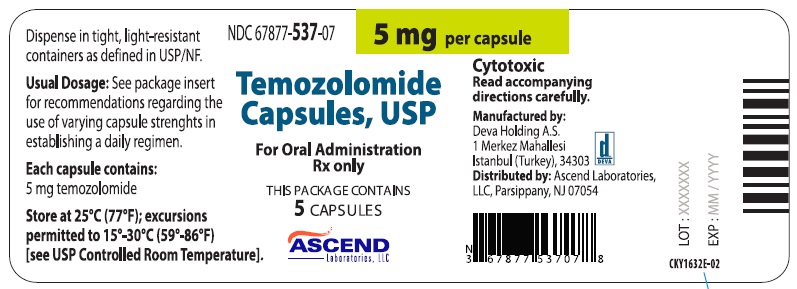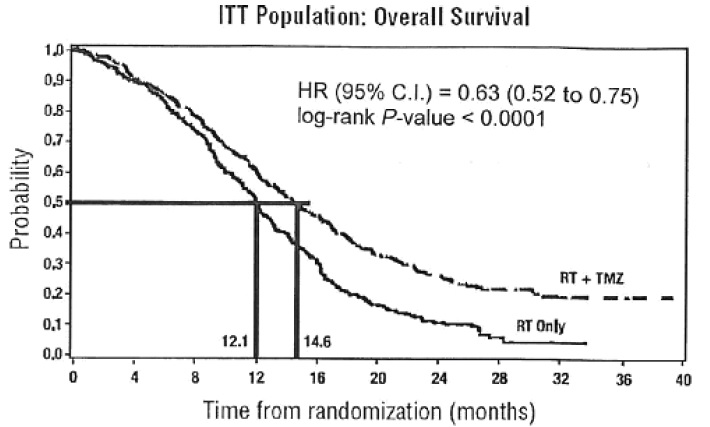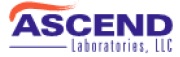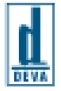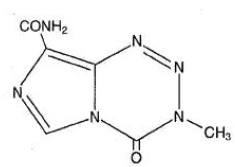 DRUG LABEL: Temozolomide
NDC: 67877-537 | Form: CAPSULE
Manufacturer: Ascend Laboratories, LLC
Category: prescription | Type: Human Prescription Drug Label
Date: 20250109

ACTIVE INGREDIENTS: TEMOZOLOMIDE 5 mg/1 1
INACTIVE INGREDIENTS: ANHYDROUS LACTOSE; SILICON DIOXIDE; SODIUM STARCH GLYCOLATE TYPE A POTATO; TARTARIC ACID; STEARIC ACID; GELATIN, UNSPECIFIED; TITANIUM DIOXIDE; FERRIC OXIDE YELLOW; FD&C BLUE NO. 2

HIGHLIGHTS OF PRESCRIBING INFORMATION

These highlights do not include all the information needed to use TEMOZOLOMIDE CAPSULES, USP safely and effectively. See full prescribing information for TEMOZOLOMIDE CAPSULES, USP.
TEMOZOLOMIDE Capsules for oral use
Initial U.S. Approval: 1999

1. INDICATIONS AND USAGE

TEMOZOLOMIDE Capsules, USP are an alkylating drug indicated for the treatment of adult patients with:
• Newly diagnosed glioblastoma concomitantly with radiotherapy and then as maintenance treatment. (1.1)
• Refractory anaplastic astrocytoma who have experienced disease progression on a drug regimen containing nitrosourea and procarbazine. (1.2)

2. DOSAGE AND ADMINISTRATION

- Administer either orally or intravenously.
- Newly Diagnosed Glioblastoma:
  o 75 mg/m^2 once daily for 42 days concomitant with focal radiotherapy followed by initial maintenance dose of 150 mg/m^2 once daily for Days 1 to 5 of each 28-day cycle for 6 cycles. May increase maintenance dose to 200 mg/ m^2 for cycles 2 – 6 based on toxicity. (2.1)
  o Provide Pneumocystis pneumonia (PCP) prophylaxis during concomitant phase and continue in patients who develop lymphopenia until resolution to grade 1 or less. (2.1)
- Refractory Anaplastic Astrocytoma: Initial dose of 150 mg/m^2 once daily on Days 1 to 5 of each 28-day cycle. (2.2)

3. DOSAGE FORMS AND STRENGTHS

· 5-mg, 20-mg, 100-mg, 140-mg, 180-mg, and 250-mg capsules. (3)

4. CONTRAINDICATIONS

History of hypersensitivity to temozolomide or any other ingredients in TEMOZOLOMIDE capsules, USP and dacarbazine.

5. WARNINGS AND PRECAUTIONS

- Myelosuppression: Monitor absolute neutrophil count (ANC) and platelet count prior to each cycle and during treatment. Geriatric patients and women have a higher risk of developing myelosuppression. (5.1)
- Myelodysplastic Syndrome and Secondary Malignancies, including myeloid leukemia, have been observed. (5.2)
- Pneumocystis Pneumonia (PCP): Closely monitor all patients, particularly those receiving steroids, for the development of lymphopenia and PCP.(5.3)
- Hepatotoxicity: Fatal and severe hepatotoxicity have been reported. Perform liver tests at baseline, midway through the first cycle, prior to each subsequent cycle, and approximately 2 to 4 weeks after the last dose of TEMOZOLOMIDE (5.4)
- Embryo-Fetal Toxicity: Can cause fetal harm. Advise females of reproductive potential of the potential risk to a fetus and to use effective contraception. Advise male patients with pregnant partners or female partners of reproductive potential to use condoms. (5.5, 8.1, 8.3)

6. ADVERSE REACTIONS

- The most common adverse reactions (≥ 20% incidence) are: alopecia, fatigue, nausea, vomiting, headache, constipation, anorexia, and convulsions. (6.1)
- The most common Grade 3 to 4 hematologic laboratory abnormalities (≥ 10% incidence) in patients with anaplastic astrocytoma are: decreased lymphocytes, decreased platelets, decreased neutrophils, and decreased leukocytes.(6.1)

To report SUSPECTED ADVERSE REACTIONS, contact Ascend Laboratories LLC at 1-877-ASC-RX01 (877-272-7901) or FDA at 1-800-FDA-1088 or www.fda.gov/medwatch.

8. USE IN SPECIFIC POPULATIONS

Lactation: Advise not to breastfeed. (8.2)

FULL PRESCRIBING INFORMATION

1. INDICATIONS AND USAGE

1.1 Newly Diagnosed Glioblastoma

TEMOZOLOMIDE Capsules, USP is indicated for the treatment of adult patients with newly diagnosed glioblastoma concomitantly with radiotherapy and then as maintenance treatment.

1.2 Refractory Anaplastic Astrocytoma

TEMOZOLOMIDE Capsules, USP is indicated for the treatment of adult patients with refractory anaplastic astrocytoma who have experienced disease progression on a drug regimen containing nitrosourea and procarbazine.

2. DOSAGE AND ADMINISTRATION

2.1 Recommended Dosage and Dosage Modifications for Newly Diagnosed Glioblastoma

Administer TEMOZOLOMIDE either orally once daily for 42 consecutive days during the concomitant phase with focal radiotherapy and then once daily on Days 1 to 5 of each 28-day cycle for 6 cycles during the maintenance phase.
Provide Pneumocystis pneumonia (PCP) prophylaxis during the concomitant phase and continue in patients who develop lymphocytopenia until resolution to grade 1 or less [see Warnings and Precautions (5.3)].
Concomitant Phase
The recommended dosage of TEMOZOLOMIDE is 75 mg/m^2 either orally or intravenously once daily for 42 days (up to 49 days) concomitant with focal radiotherapy (60 Gy administered in 30 fractions). Focal radiotherapy includes the tumor bed or resection site with a 2- to 3-cm margin.
Obtain a complete blood count weekly. No dose reductions are recommended during the concomitant phase. The recommended dosage modifications during the concomitant phase are provided in Table 1.
TABLE 1: Temozolomide Dosage Modifications During Concomitant Phase

Adverse Reaction | Interruption | Discontinuation
Absolute Neutrophil Count | Withhold TEMOZOLOMIDE if ANC is greater than or equal to 0.5 x 10^9/L and less than 1.5 x 10^9/L. Resume TEMOZOLOMIDE when ANC is greater than or equal to 1.5 x 10^9/L. | Discontinue TEMOZOLOMIDE if platelet count is less than 0.5 x 10^9/L.
Platelet Count | Withhold TEMOZOLOMIDE if platelet count is greater than or equal to 10 x 10^9/L and less than 100 x 10^9/L. Resume TEMOZOLOMIDE when platelet count is greater than or equal to 100 x 10^9/L. | Discontinue TEMOZOLOMIDE if platelet count is less than 10 x 10^9/L.
Non-hematological Adverse Reaction (except for alopecia, nausea, vomiting) | Withhold TEMOZOLOMIDE if Grade 2 adverse reaction occurs. Resume TEMOZOLOMIDE when resolution to Grade 1 or less. | Discontinue TEMOZOLOMIDE if Grade 3 or 4 adverse reaction occurs.

Maintenance Phase
Beginning 4 weeks after Concomitant Phase completion, administer TEMOZOLOMIDE either orally or intravenously once daily on Days 1 to 5 of each 28-day cycle for 6 cycles. The recommended dosage of TEMOZOLOMIDE is as follows:
• Cycle 1: 150 mg/m^2 per day
• Cycles 2 to 6: May increase to 200 mg/m^2 per day if the following conditions are met before starting cycle 2. If the dose was not escalated at the onset of Cycle 2, do not increase the dose for Cycles 3 to 6.
o Nonhematologic toxicity is grade 2 or less (except for alopecia, nausea, and vomiting)
o ANC is greater than or equal to 1.5 x 10^9/L and
o Platelet count is greater than or equal to 100 x 10^9/L.
Obtain a complete blood count on Day 22 and then weekly until the ANC is above 1.5 x 10^9/L and the platelet count is above 100 x 10^9/L. Do not start the next cycle until the ANC and platelet count exceed these levels.
The recommended dosage modifications during the maintenance phase are provided in Table 2. If TEMOZOLOMIDE is withheld, reduce the dose for the next cycle by 50 mg/m^2 per day. Permanently discontinue TEMOZOLOMIDE in patients who are unable to tolerate a dose of 100 mg/m^2 per day.
TABLE 2: Temozolomide Dosage Modifications During Maintenance Treatment

Toxicity | Interruption | Discontinuation
Absolute Neutrophil Count | Withhold TEMOZOLOMIDE if ANC less than 1 x 10^9/L. When ANC is above 1.5 x 10^9/L, resume TEMOZOLOMIDE at reduced dose for the next cycle. | Unable to tolerate a dose of 100 mg/m^2 per day.
Platelet Count | Withhold TEMOZOLOMIDE if platelet less than 50 x 10^9/L. When platelet count is above 100 x 10^9/L, resume TEMOZOLOMIDE at reduced dose for the next cycle. | Unable to tolerate a dose of 100 mg/m^2 per day.
Non-hematological Adverse Reaction (except for alopecia, nausea, vomiting) | Withhold TEMOZOLOMIDE if Grade 3 adverse reaction. When resolved to grade 1 or less, resume TEMOZOLOMIDE at reduced dose for the next cycle. | Recurrent Grade 3 after dose reduction. Grade 4 Unable to tolerate a dose of 100 mg/m^2 per day.

2.2 Recommended Dosage and Dosage Modifications for Refractory Anaplastic Astrocytoma

The recommended initial dosage of TEMOZOLOMIDE is 150 mg/m^2 once daily on Days 1 to 5 of each 28-day cycle. Increase the TEMOZOLOMIDE dose to 200 mg/m^2 per day if the following conditions are met at the nadir and on Day 1 of the next cycle:
• ANC is greater than or equal to 1.5 x 10^9/L and
• Platelet count is greater than or equal to 100 x 10^9/L
Continue TEMOZOLOMIDE until disease progression or unacceptable toxicity. In the clinical trial, treatment could be continued for a maximum of 2 years, but the optimum duration of therapy is not known.
Obtain a complete blood count on Day 22 and then weekly until the ANC is above 1.5 x 10^9/L and the platelet count is above 100 x 10^9/L. Do not start the next cycle until the ANC and platelet count exceed these levels.
If the ANC is less than 1 x 10^9/L or the platelet count is less than 50 x 10^9/L during any cycle, reduce the TEMOZOLOMIDE dose for the next cycle by 50 mg/m^2 per day. Permanently discontinue TEMOZOLOMIDE in patients who are unable to tolerate a dose of 100 mg/m^2 per day.

2.3 Preparation and Administration

TEMOZOLOMIDE is a cytotoxic drug. Follow applicable special handling and disposal procedures^1.
TEMOZOLOMIDE capsules
Administer TEMOZOLOMIDE consistently with respect to food (fasting vs.nonfasting) [see Clinical Pharmacology12.3)]. To reduce nausea and vomiting, take TEMOZOLOMIDE on an empty stomach or at bedtime and consider antiemetic therapy prior to and/or following TEMOZOLOMIDE administration.
Swallow TEMOZOLOMIDE capsules whole. Do not open or chew capsules.

If capsules are accidentally opened or damaged, take precautions to avoid inhalation or contact with the skin or mucous membranes. In case of powder
contact, the hands should be washed.

3. DOSAGE FORMS AND STRENGTHS

· TEMOZOLOMIDE Capsules, USP for oral administration

5-mg: Capsules have opaque white bodies with opaque green caps. The capsule body is imprinted with the dosage strength.
20-mg: Capsules have opaque white bodies with opaque yellow caps. The capsule body is imprinted with the dosage strength.
100-mg: Capsules have opaque white bodies with opaque flesh caps. The capsule body is imprinted with the dosage strength.
140-mg: Capsules have opaque white bodies with transparent blue caps. The capsule body is imprinted with the dosage strength.
180-mg: Capsules have opaque white bodies with opaque orange caps. The capsule body is imprinted with the dosage strength.
250-mg: Capsules have opaque white bodies with opaque white caps. The capsule body is imprinted with the dosage strength.

4. CONTRAINDICATIONS

TEMOZOLOMIDE is contraindicated in patients with a history of hypersensitivity reactions to:
• temozolomide or any other ingredients in TEMOZOLOMIDE; and
• dacarbazine, since both temozolomide and dacarbazine are metabolized to the same active metabolite 5-(3-methyltriazen-1-yl)-imidazole-4-carboxamide.
Reactions to TEMOZOLOMIDE have included anaphylaxis [see Adverse Reactions (6.2)].

5. WARNINGS AND PRECAUTIONS

5.1 Myelosuppression

Myelosuppression, including pancytopenia, leukopenia and anemia, some with fatal outcomes, have occurred with TEMOZOLOMIDE [see Adverse Reactions (6.1, 6.2)]. Geriatric patients and women have been shown in clinical trials to have a higher risk of developing myelosuppression.
Prior to dosing, patients must have an ANC of 1.5 x 10^9/L or greater and a platelet count of 100 x 10^9/L or greater.
For the concomitant phase with radiotherapy, obtain a complete blood count prior to initiation of treatment and weekly during treatment [see Dosage and Administration (2.1)].
For the 28-day treatment cycles, obtain a complete blood count prior to treatment on Day 1 and on Day 22 of each cycle. Perform complete blood counts weekly until recovery if the ANC falls below 1.5 x 10^9/L and the platelet count falls below 100 x 10^9/L [see Dosage and Administration (2.1, 2.2)].

5.2 Myelodysplastic Syndrome and Secondary Malignancies

Cases of myelodysplastic syndrome and secondary malignancies, including myeloid leukemia, have been observed following TEMOZOLOMIDE administration.

5.3 Pneumocystis Pneumonia

Pneumocystis pneumonia (PCP) can occur in patients receiving TEMOZOLOMIDE. The risk of PCP is increased in patients receiving steroids or with longer treatment regimens.
For patients with newly diagnosed glioblastoma, provide PCP prophylaxis for all patients during the concomitant phase. Continue in patients who experience lymphopenia until resolution to grade 1 or less [see Dosage and Administration (2.1)].
Monitor all patients receiving TEMOZOLOMIDE for the development of lymphopenia and PCP.

5.4 Hepatotoxicity

Fatal and severe hepatotoxicity have been reported in patients receiving TEMOZOLOMIDE. Perform liver tests at baseline, midway through the first cycle, prior to each subsequent cycle, and approximately 2 to 4 weeks after the last dose of TEMOZOLOMIDE.

5.5 Embryo-Fetal Toxicity

Based on findings from animal studies and its mechanism of action, TEMOZOLOMIDE can cause fetal harm when administered to a pregnant woman. Adverse developmental outcomes have been reported in both pregnant patients and pregnant partners of male patients. Oral administration of temozolomide to rats and rabbits during the period of organogenesis resulted in embryolethality and polymalformations at doses less than the maximum human dose based on body surface area.
Advise pregnant women of the potential risk to the fetus. Advise females of reproductive potential to use effective contraception during treatment with TEMOZOLOMIDE and for at least 6 months after the final dose. Because of potential risk of genotoxic effects on sperm, advise male patients with female partners of reproductive potential to use condoms during treatment with TEMOZOLOMIDE and for at least 3 months after the final dose. Advise male patients not to donate semen during treatment with TEMOZOLOMIDE and for at least 3 months after the final dose [see Use in Specific Populations (8.1, 8.3)].

6. ADVERSE REACTIONS

The following clinically significant adverse reactions are described elsewhere in the labeling:
• Myelosuppression [see Warnings and Precautions (5.1)].
• Myelodysplastic Syndrome and Secondary Malignancies [see Warnings and Precautions (5.2)].
• Pneumocystis Pneumonia [see Warnings and Precautions (5.3)].
• Hepatotoxicity [see Warnings and Precautions (5.4)].

6.1 Clinical Trials Experience

Because clinical trials are conducted under widely varying conditions, adverse reaction rates observed in the clinical trials of a drug cannot be directly compared to rates in the clinical trials of another drug and may not reflect the rates observed in practice.

Newly Diagnosed Glioblastoma
The safety of TEMOZOLOMIDE was evaluated in Study MK-7365-051 [see Clinical Studies (14.1)].
Forty-nine percent (49%) of patients treated with TEMOZOLOMIDE reported one or more severe or life-threatening reactions, most commonly fatigue (13%), convulsions (6%), headache (5%), and thrombocytopenia (5%).
The most common adverse reactions (≥20%) across the cumulative TEMOZOLOMIDE experience were alopecia, fatigue, nausea, and vomiting. Table 3 summarizes the adverse reactions in Newly Diagnosed Glioblastoma Trial. Overall, the pattern of reactions during the maintenance phase was consistent with the known safety profile of TEMOZOLOMIDE.
TABLE 3: Adverse Reactions (≥5%) in Patients Receiving TEMOZOLOMIDE in Newly Diagnosed Glioblastoma Trial

Adverse Reactions | Concomitant Phase |  |  |  | Maintenance Phase
Adverse Reactions | Radiation Therapy and TEMOZOLAMIDE N=288* |  | Radiation Therapy Alone N=285 |  | TEMOZOLOMIDE N=224
Adverse Reactions | All Grades (%) | Grade ≥3 (%) | All Grades (%) | Grade ≥3 (%) | All Grades (%) | Grade ≥3 (%)
Skin and Subcutaneous Tissue
Alopecia | 69 |  | 63 |  | 55
Rash | 19 | 1 | 15 |  | 13 | 1
Dry Skin | 2 |  | 2 |  | 5 | <1
Pruritus | 4 |  | 1 |  | 5
Erythema | 5 |  | 5 |  | 1
General
Fatigue | 54 | 7 | 49 | 5 | 61 | 9
Anorexia | 19 | 1 | 9 | <1 | 27 | 1
Headache | 19 | 2 | 17 | 4 | 23 | 4
Weakness | 3 | 2 | 3 | 1 | 7 | 2
Dizziness | 4 | 1 | 4 |  | 5
Gastrointestinal System
Nausea | 36 | 1 | 16 | <1 | 49 | 1
Vomiting | 20 | <1 | 6 | <1 | 29 | 2
Constipation | 18 | 1 | 6 |  | 22
Diarrhea | 6 |  | 3 |  | 10 | 1
Stomatitis | 7 |  | 5 | <1 | 9 | 1
Abdominal Pain | 2 | <1 | 1 |  | 5 | <1
Eye
Vision Blurred | 9 | 1 | 9 | 1 | 8
Injury
Radiation Injury NOS | 7 |  | 4 | <1 | 2
Central and Peripheral Nervous System
Convulsions | 6 | 3 | 7 | 3 | 11 | 3
Memory Impairment | 3 | <1 | 4 | <1 | 7 | 1
Confusion | 4 | 1 | 4 | 2 | 5 | 2
Special Senses Other
Taste Perversion | 6 |  | 2 |  | 5
Respiratory System
Coughing | 5 | 1 | 1 |  | 8 | <1
Dyspnea | 4 | 2 | 3 | 1 | 5 | <1
Psychiatric
Insomnia | 5 |  | 3 | <1 | 4
Immune System
Allergic Reaction | 5 |  | 2 | <1 | 3
Platelet, Bleeding and Clotting
Thrombocytopenia | 4 | 3 | 1 |  | 8 | 4
Musculoskeletal System
Arthralgia | 2 | <1 | 1 |  | 6

*One patient who was randomized to radiation therapy only arm received radiation therapy and TEMOZOLOMIDE. NOS=not otherwise specified.
Note: Grade 5 (fatal) adverse reactions are included in the Grade ≥3 column.
When laboratory abnormalities and adverse reactions were combined, Grade 3 or Grade 4 neutrophil abnormalities including neutropenic reactions were observed in 8% of patients, and Grade 3 or Grade 4 platelet abnormalities including thrombocytopenic reactions, were observed in 14% of patients.
Refractory Anaplastic Astrocytoma
The safety of TEMOZOLOMIDE was evaluated in Study MK-7365-006 [see Clinical Studies (14.2)].
Myelosuppression (thrombocytopenia and neutropenia) was the dose-limiting adverse reaction. It usually occurred within the first few cycles of therapy and was not cumulative. Myelosuppression occurred late in the treatment cycle and returned to normal, on average, within 14 days of nadir counts. The median nadirs occurred at 26 days for platelets (range: 21-40 days) and 28 days for neutrophils (range: 1-44 days). Only 14% (22/158) of patients had a neutrophil nadir and 20% (32/158) of patients had a platelet nadir, which may have delayed the start of the next cycle. Less than 10% of patients required hospitalization, blood transfusion, or discontinuation of therapy due to myelosuppression.
The most common adverse reactions (≥20%) were nausea, vomiting, headache, fatigue, constipation, and convulsions.
Tables 4 and 5 summarize the adverse reactions and hematological laboratory abnormalities in Refractory Anaplastic Astrocytoma Trial.
TABLE 4: Adverse Reactions (≥5%) in Patients Receiving TEMOZOLOMIDE in Refractory Anaplastic Astrocytoma Trial

Adverse Reactions | TEMOZOLOMIDE N=158
 | All Reactions (%) |  | Grades 3-4 (%)
Gastrointestinal System
Nausea | 53 | 10
Vomiting | 42 | 6
Constipation | 33 | 1
Diarrhea | 16 | 2
Abdominal pain | 9 | 1
Anorexia | 9 | 1
General
Headache | 41 | 6
Fatigue | 34 | 4
Asthenia | 13 | 6
Fever | 13 | 2
Back pain | 8 | 3
Central and Peripheral Nervous System
Convulsions | 23 | 5
Hemiparesis | 18 | 6
Dizziness | 12 | 1
Coordination abnormal | 11 | 1
Amnesia | 10 | 4
Insomnia | 10
Paresthesia | 9 | 1
Somnolence | 9 | 3
Paresis | 8 | 3
Urinary incontinence | 8 | 2
Ataxia | 8 | 2
Dysphasia | 7 | 1
Convulsions local | 6
Gait abnormal | 6 | 1
Confusion | 5
Cardiovascular
Edema peripheral | 11 | 1
Resistance Mechanism
Infection viral | 11
Endocrine
Adrenal hypercorticism | 8
Respiratory System
Upper respiratory tract infection | 8
Pharyngitis | 8
Sinusitis | 6
Coughing | 5
Skin and Appendages
Rash | 8
Pruritus | 8 | 1
Urinary System
Urinary tract infection | 8
Micturition increased frequency | 6
Psychiatric
Anxiety | 7 | 1
Depression | 6
Reproductive Disorders
Breast pain, female | 6
Metabolic
Weight increase | 5
Musculoskeletal System
Myalgia | 5
Vision
Diplopia | 5
Vision abnormal* | 5

*This term includes blurred vision; visual deficit; vision changes; and vision troubles.
TABLE 5: Grade 3 to 4 Adverse Hematologic Laboratory Abnormalities in Refractory Anaplastic Astrocytoma Trial

 | TEMOZOLOMIDE *,†
Decreased lymphocytes | 55%
Decreased platelets | 19%
Decreased neutrophils | 14%
Decreased leukocytes | 11%
Decreased hemoglobin | 4%

*Change from Grade 0 to 2 at baseline to Grade 3 or 4 during treatment.
†Denominator range= 142, 158
Hematological Toxicities for Advanced Gliomas:
In clinical trial experience with 110 to 111 females and 169 to 174 males (depending on measurements), females experienced higher rates of Grade 4 neutropenia (ANC < 0.5 x 10^9/L) and thrombocytopenia (< 20 x 10^9/L) than males in the first cycle of therapy (12% vs. 5% and 9% vs. 3%, respectively).
In the entire safety database for which hematologic data exist (N=932), 7% (4/61) and 9.5% (6/63) of patients > 70 years experienced Grade 4 neutropenia or thrombocytopenia in the first cycle, respectively. For patients ≤ 70 years, 7% (62/871) and 5.5% (48/879) experienced Grade 4 neutropenia or thrombocytopenia in the first cycle, respectively. Pancytopenia, leukopenia, and anemia also occurred.
Adverse reactions with TEMOZOLOMIDE for injection
Adverse reactions that were reported in 35 patients who received TEMOZOLOMIDE for injection that were not reported in patients who received TEMOZOLOMIDE capsules were pain, irritation, pruritus, warmth, swelling, and erythema at infusion site; petechiae; and hematoma.

6.2 Postmarketing Experience

The following adverse reactions have been identified during post-approval use of TEMOZOLOMIDE. Because these reactions are reported voluntarily from a population of uncertain size, it is not always possible to reliably estimate their frequency or establish a causal relationship to the drug exposure.

Dermatologic: Toxic epidermal necrolysis and Stevens-Johnson syndrome

Immune System: Hypersensitivity reactions, including anaphylaxis. Erythema multiforme, which resolved after discontinuation of TEMOZOLOMIDE and, in some cases, recurred upon rechallenge.

Hematopoietic: Prolonged pancytopenia, which may result in aplastic anemia and fatal outcomes.

Hepatobiliary: Fatal and severe hepatotoxicity, elevation of liver enzymes, hyperbilirubinemia, cholestasis, and hepatitis

Infections: Serious opportunistic infections, including some cases with fatal outcomes, with bacterial, viral (primary and reactivated), fungal, and protozoan organisms.
Pulmonary:Interstitial pneumonitis, pneumonitis, alveolitis, and pulmonary fibrosis.

Endocrine: Diabetes insipidus

8. USE IN SPECIFIC POPULATIONS

8.1 Pregnancy

Risk Summary
Based on its mechanism of action [see Clinical Pharmacology (12.1)] and findings from animal studies, TEMOZOLOMIDE can cause fetal harm when administered to a pregnant woman. Available postmarketing reports describe cases of spontaneous abortions and congenital malformations, including polymalformations with central nervous system, facial, cardiac, skeletal, and genitourinary system anomalies with exposure to TEMOZOLOMIDE during pregnancy. These cases report similar adverse developmental outcomes to those observed in animal studies. Administration of TEMOZOLOMIDE to rats and rabbits during the period of organogenesis caused numerous external, internal, and skeletal malformations at doses less than the maximum human dose based on body surface area (see Data). Advise pregnant women of the potential risk to a fetus.
In the U.S. general population, the estimated background risk of major birth defects and miscarriage in clinically recognized pregnancies is 2% to 4% and 15% to 20%, respectively.
Data
Animal Data
Five consecutive days of oral administration of temozolomide at doses of 75 and 150 mg/m^2 (0.38 and 0.75 times the human dose of 200 mg/m^2) in rats and rabbits, respectively, during the period of organogenesis (Gestation Days 8-12) caused numerous malformations of the external and internal organs and skeleton in both species. In rabbits, temozolomide at the 150 mg/m^2 dose (0.75 times the human dose of 200 mg/m2) caused embryolethality as indicated by increased resorptions.

8.2 Lactation

There are no data on the presence of TEMOZOLOMIDE or its metabolites in human milk, the effects on a breastfed child, or the effects on milk production. Because of the potential for serious adverse reactions, including myelosuppression from temozolomide in the breastfed children, advise women not to breastfeed during treatment with TEMOZOLOMIDE and for at least 1 week after the final dose.

8.3 Females and Males of Reproductive Potential

Pregnancy Testing
Verify pregnancy status in females of reproductive potential prior to initiating TEMOZOLOMIDE [see Use in Specific Populations (8.1)].
Contraception
Females
TEMOZOLOMIDE can cause embryo-fetal harm when administered to a pregnant woman [see Use in Specific Populations (8.1)]. Advise females of reproductive potential to use effective contraception during treatment with TEMOZOLOMIDE and for at least 6 months after the last dose.
Males
Because of the potential for embryofetal toxicity and genotoxic effects on sperm cells, advise male patients with pregnant partners or female partners of reproductive potential to use condoms during treatment with TEMOZOLOMIDE and for at least 3 months after the final dose [see Use in Specific Populations (8.1), Nonclinical Toxicology (13.1)].
Advise male patients not to donate semen during treatment with TEMOZOLOMIDE and for at least 3 months after the final dose.
Infertility
TEMOZOLOMIDE may impair male fertility [see Nonclinical Toxicology (13.1)]. Limited data from male patients show changes in sperm parameters during treatment with TEMOZOLOMIDE; however, no information is available on the duration or reversibility of these changes.

8.4 Pediatric Use

Safety and effectiveness of TEMOZOLOMIDE have not been established in pediatric patients. Safety and effectiveness of TEMOZOLOMIDE capsules were assessed, but not established, in 2 open-label studies in pediatric patients aged 3 to18 years. In one study, 29 patients with recurrent brain stem glioma and 34 patients with recurrent high-grade astrocytoma were enrolled. In a second study conducted by the Children’s Oncology Group (COG), 122 patients were enrolled, including patients with medulloblastoma/PNET (29), high grade astrocytoma (23), low grade astrocytoma (22), brain stem glioma (16), ependymoma (14), other CNS tumors (9), and non-CNS tumors (9). The adverse reaction profile in pediatric patients was similar to adults.

8.5 Geriatric Use

In the Newly Diagnosed Glioblastoma trial, Study MK-7365-051, 15% of patients were 65 years and older. This study did not include sufficient numbers of patients aged 65 years and older to determine differences in effectiveness from younger patients. No overall differences in safety were observed between patients ≥65 years and younger patients.
In the Refractory Anaplastic Astrocytoma trial, Study MK-7365-0006, 4% of patients were 70 years and older. This study did not include sufficient numbers of patients aged 70 years and older to determine differences in effectiveness from younger patients. Patients 70 years and older had a higher incidence of Grade 4 neutropenia (25%) and Grade 4 thrombocytopenia (20%) in the first cycle of therapy than patients less than 70 years of age [see Warnings and Precautions (5.1), Adverse Reactions (6.1)].

8.6 Renal Impairment

No dosage adjustment is recommended for patients with creatinine clearance (CLcr) of 36 to 130 mL/min/m^2 [see Clinical Pharmacology (12.3)]. The recommended dose of TEMOZOLOMIDE has not been established for patients with severe renal impairment (CLcr < 36 mL/min/m^2) or for patients with end-stage renal disease on dialysis.

8.7 Hepatic Impairment

No dosage adjustment is recommended for patients with mild to moderate hepatic impairment (Child Pugh class A and B) [see Clinical Pharmacology (12.3)]. The recommended dose of TEMOZOLOMIDE has not been established for patients with severe hepatic impairment (Child-Pugh class C).

10. OVERDOSAGE

Dose-limiting toxicity was myelosuppression and was reported with any dose but is expected to be more severe at higher doses. An overdose of 2000 mg per day for 5 days was taken by one patient and the adverse reactions reported were pancytopenia, pyrexia, multi-organ failure, and death. There are reports of patients who have taken more than 5 days of treatment (up to 64 days), with adverse reactions reported including myelosuppression, which in some cases was severe and prolonged, and infections and resulted in death. In the event of an overdose, monitor complete blood count and provide supportive measures as necessary.

11. DESCRIPTION

Temozolomide is an alkylating drug. The chemical name of temozolomide is 3,4-dihydro-3-methyl-4-oxoimidazo[5,1-d]-as-tetrazine-8-carboxamide. The structural formula of temozolomide is:

The material is a white to light tan/light pink powder with a molecular formula of C6H6N6O2 and a molecular weight of 194.15. The molecule is stable at acidic pH (<5) and labile at pH >7; hence TEMOZOLOMIDE can be administered orally and intravenously. The prodrug, temozolomide, is rapidly hydrolyzed to the active 5-(3-methyltriazen-1-yl) imidazole-4-carboxamide (MTIC) at neutral and alkaline pH values, with hydrolysis taking place even faster at alkaline pH.

TEMOZOLOMIDE Capsules, USP:

Each capsule for oral use contains either 5 mg, 20 mg, 100 mg, 140 mg, 180 mg, or 250 mg of temozolomide.

The inactive ingredients for TEMOZOLOMIDE Capsules, USP are as follows:

· TEMOZOLOMIDE 5 mg: lactose anhydrous (132.8 mg), colloidal silicon dioxide (0.2 mg), sodium starch glycolate (7.5 mg), tartaric acid (1.5 mg), and stearic acid (3.0 mg).

·TEMOZOLOMIDE 20 mg: lactose anhydrous (182.2 mg), colloidal silicon dioxide (0.2 mg), sodium starch glycolate (11 mg), tartaric acid (2.2 mg), and stearic acid (4.4 mg).

·TEMOZOLOMIDE 100 mg: lactose anhydrous (175.7 mg), colloidal silicon dioxide (0.3 mg), sodium starch glycolate (15 mg), tartaric acid (3.0 mg), and stearic acid (6.0 mg).

·TEMOZOLOMIDE 140 mg: lactose anhydrous (246 mg), colloidal silicon dioxide (0.4 mg), sodium starch glycolate (21 mg), tartaric acid (4.2 mg), and stearic acid (8.4 mg).

·TEMOZOLOMIDE 180 mg: lactose anhydrous (316.3 mg), colloidal silicon dioxide (0.5 mg), sodium starch glycolate (27 mg), tartaric acid (5.4 mg), and stearic acid (10.8 mg).

· TEMOZOLOMIDE 250 mg: lactose anhydrous (154.3 mg), colloidal silicon dioxide (0.7 mg), sodium starch glycolate (22.5 mg), tartaric acid (9.0 mg), and stearic acid (13.5 mg).

The body of the capsules is made of gelatin and titanium dioxide and is opaque white. The cap is also made of gelatin and the colors may vary based on the dosage strength. The capsule body and cap are imprinted with pharmaceutical branding ink, which contains shellac, dehydrated alcohol, isopropyl alcohol, butyl alcohol, propylene glycol, purified water, strong ammonia solution, potassium hydroxide, and ferric oxide.

· TEMOZOLOMIDE 5 mg: The opaque green cap contains gelatin, titanium dioxide, iron oxide yellow and FD&C Blue 2.

·TEMOZOLOMIDE 20 mg: The opaque yellow cap contains gelatin, titanium dioxide and iron oxide yellow.

·TEMOZOLOMIDE 100 mg: The opaque flesh cap contains gelatin, titanium dioxide and iron oxide red.

·TEMOZOLOMIDE 140 mg: The transparent blue cap contains gelatin, FD&C Blue #2, and titanium dioxide.

· TEMOZOLOMIDE 180 mg: The opaque orange cap contains gelatin, titanium dioxide and iron oxide red.

·TEMOZOLOMIDE 250 mg: The opaque white cap contains gelatin and titanium dioxide.

12. CLINICAL PHARMACOLOGY

12.1 Mechanism of Action

Temozolomide is not directly active but undergoes rapid nonenzymatic conversion at physiologic pH to the reactive compound 5-(3-methyltriazen-1-yl)-imidazole-4-carboxamide (MTIC). The cytotoxicity of MTIC is thought to be primarily due to alkylation of DNA. Alkylation (methylation) occurs mainly at the O^6 and N^7 positions of guanine.

12.3 Pharmacokinetics

Following a single oral dose of 150 mg/m^2, the mean Cmax value for temozolomide was 7.5 mcg/mL and for MTIC was 282 ng/mL. The mean AUC value for temozolomide was 23.4 mcg·hr/mL and for MTIC was 864 ng·hr/mL. Following a single 90-minute intravenous infusion of 150 mg/m^2, the mean Cmax value for temozolomide was 7.3 mcg/mL and for MTIC was 276 ng/mL. The mean AUC value for temozolomide was 24.6 mcg·hr/mL and for MTIC was 891 ng·hr/mL. Temozolomide exhibits linear kinetics over the therapeutic dosing range of 75 mg/m^2/day to 250 mg/m^2/day.
Absorption
The median Tmax is 1 hour.
Effect of Food
The mean Cmax and AUC decreased by 32% and 9%, respectively, and median Tmax increased by 2-fold (from 1-2.25 hours) when TEMOZOLOMIDE capsules were administered after a modified high-fat breakfast (587 calories comprised of 1 fried egg, 2 strips of bacon, 2 slices of toast, 2 pats of butter, and 8 oz whole milk).

Distribution
Temozolomide has a mean apparent volume of distribution of 0.4 L/kg (%CV = 13%). The mean percent bound of drug-related total radioactivity is 15%.

Elimination
Clearance of temozolomide is about 5.5 L/hr/m^2 and the mean elimination half-life is 1.8 hours.
Metabolism
Temozolomide is spontaneously hydrolyzed at physiologic pH to the active species, MTIC and to temozolomide acid metabolite. MTIC is further hydrolyzed to 5-amino-imidazole-4-carboxamide (AIC), which is known to be an intermediate in purine and nucleic acid biosynthesis, and to methylhydrazine, which is believed to be the active alkylating species. Cytochrome P450 enzymes play only a minor role in the metabolism of temozolomide and MTIC. Relative to the AUC of temozolomide, the exposure to MTIC and AIC is 2.4% and 23%, respectively.
Excretion
About 38% of the administered temozolomide total radioactive dose is recovered over 7 days: 38% in urine and 0.8% in feces. The majority of the recovery of radioactivity in urine is unchanged temozolomide (6%), AIC (12%), temozolomide acid metabolite (2.3%), and unidentified polar metabolite(s) (17%).
Specific Populations
No clinically meaningful differences in the pharmacokinetics of temozolomide were observed based on age (range: 19-78 years), gender, smoking status (smoker vs. non-smoker), creatinine clearance (CLcr) of 36 to 130 mL/min/m^2, or mild to moderate hepatic impairment (Child Pugh class A and B). The pharmacokinetics of temozolomide has not been studied in patients with CLcr < 36 mL/min/m^2, end-stage renal disease on dialysis, or severe hepatic impairment (Child-Pugh class C).
Drug Interaction Studies
Effect of Other Drugs on Temozolomide Pharmacokinetics
In a multiple-dose study, administration of TEMOZOLOMIDE Capsules with ranitidine did not change the Cmax or AUC values for temozolomide or MTIC.
A population analysis indicated that administration of valproic acid decreases the clearance of temozolomide by about 5%.
A population analysis did not demonstrate any influence of coadministered dexamethasone, prochlorperazine, phenytoin, carbamazepine, ondansetron, histamine-2-receptor antagonists, or phenobarbital on the clearance of orally administered TEMOZOLOMIDE.

13. NONCLINICAL TOXICOLOGY

13.1 Carcinogenesis, Mutagenesis, Impairment of Fertility

Temozolomide is carcinogenic in rats at doses less than the maximum recommended human dose. Temozolomide induced mammary carcinomas in both males and females at doses 0.13 to 0.63 times the maximum human dose (25 - 125 mg/ m^2) when administered orally on 5 consecutive days every 28-days for 6 cycles. Temozolomide also induced fibrosarcomas of the heart, eye, seminal vesicles, salivary glands, abdominal cavity, uterus, and prostate, carcinomas of the seminal vesicles, schwannomas of the heart, optic nerve, and harderian gland, and adenomas of the skin, lung, pituitary, and thyroid at doses 0.5 times the maximum daily dose. Mammary tumors were also induced following 3 cycles of temozolomide at the maximum recommended daily dose.

Temozolomide is a mutagen and a clastogen. In a reverse bacterial mutagenesis assay (Ames assay), temozolomide increased revertant frequency in the absence and presence of metabolic activation. Temozolomide was clastogenic in human lymphocytes in the presence and absence of metabolic activation.

Temozolomide impairs male fertility. Temozolomide caused syncytial cells/immature sperm formation at doses of 50 and 125 mg/m^2 (0.25 and 0.63 times the human dose of 200 mg/m^2) in rats and dogs, respectively, and testicular atrophy in dogs at 125 mg/m^2.

13.2 Animal Toxicology and/or Pharmacology

Toxicology studies in rats and dogs identified a low incidence of hemorrhage, degeneration, and necrosis of the retina at temozolomide doses equal to or greater than 125 mg/m2 (0.63 times the human dose of 200 mg/m^2). These changes were most commonly seen at doses where mortality was observed.

14. CLINICAL STUDIES

14.1 Newly Diagnosed Glioblastoma

The efficacy of TEMOZOLOMIDE was evaluated in Study MK-7365-051, a randomized (1:1), multicenter, open-label trial. Eligible patients were required to have newly diagnosed glioblastoma. Patients were randomized to receive either radiation therapy alone or concomitant TEMOZOLOMIDE 75 mg/m^2 once daily starting the first day of radiation therapy and continuing until the last day of radiation therapy for 42 days (with a maximum of 49 days), followed by TEMOZOLOMIDE 150 mg/m^2 or 200 mg/m^2 once daily on Days 1 to 5 of each 28-day cycle, starting 4 weeks after the end of radiation therapy and continuing for 6 cycles. In both arms, focal radiation therapy was delivered as 60 Gy/30 fractions and included radiation to the tumor bed or resection site with a 2- to 3-cm margin. PCP prophylaxis was required during the concomitant phase, regardless of lymphocyte count and continued until recovery of lymphocyte count to grade 1 or less. The major efficacy outcome measure was overall survival.
A total of 573 patients were randomized, 287 to TEMOZOLOMIDE and radiation therapy and 286 to radiation therapy alone. At the time of disease progression, TEMOZOLOMIDE was administered as salvage therapy in 161 patients of the 282 (57%) in the radiation therapy alone arm and 62 patients of the 277 (22%) in the TEMOZOLOMIDE and radiation therapy arm.
The addition of concomitant and maintenance TEMOZOLOMIDE to radiation therapy for the treatment of patients with newly diagnosed glioblastoma showed a statistically significant improvement in overall survival compared to radiotherapy alone (Figure 1). The hazard ratio (HR) for overall survival was 0.63 (95% CI: 0.52, 0.75) with a log-rank P<0.0001 in favor of the TEMOZOLOMIDE arm. The median survival was increased by 2.5 months in the TEMOZOLOMIDE arm.

FIGURE 1: Kaplan-Meier Curves for Overall Survival (ITT Population) in Newly Diagnosed Glioblastoma Trial

14.2 Refractory Anaplastic Astrocytoma

The efficacy of TEMOZOLOMIDE was evaluated in Study MK-7365-006, a single-arm, multicenter trial. Eligible patients had anaplastic astrocytoma at first relapse and a baseline Karnofsky performance status (KPS) of 70 or greater. Patients had previously received radiation therapy and may also have previously received a nitrosourea with or without other chemotherapy. Fifty-four patients had disease progression on prior therapy with both a nitrosourea and procarbazine and their malignancy was considered refractory to chemotherapy (refractory anaplastic astrocytoma population). TEMOZOLOMIDE capsules were given on Days 1 to 5 of each 28-day cycle at a starting dose of 150 mg/m^2/day. If ANC was ≥1.5 x 10^9/L and platelet count was ≥100 x 10^9/L at the nadir and on Day 1 of the next cycle, the TEMOZOLOMIDE dose was increased to 200 mg/m^2/day. The major efficacy outcome measure was progression-free survival at 6 months and the additional efficacy outcome measures were overall survival and overall response rate.
In the refractory anaplastic astrocytoma population (n=54), the median age was 42 years (range: 19 to 76); 65% were male; and 72% had a KPS of >80. 63% of patients had surgery other than a biopsy at the time of initial diagnosis. Of those patients undergoing resection, 73% underwent a subtotal resection and 27% underwent a gross total resection. 18% of patients had surgery at the time of first relapse. The median time from initial diagnosis to first relapse was 13.8 months (range: 4.2 months to 6.3 years).

In the refractory anaplastic astrocytoma population, the overall response rate (CR + PR) was 22% (12 of 54 patients) and the complete response rate was 9% (5 of 54 patients). The median duration of all responses was 50 weeks (range: 16 to 114 weeks) and the median duration of complete responses was 64 weeks (range: 52 to 114 weeks). In this population, progression-free survival at 6 months was 45% (95% CI: 31%, 58%) and progression-free survival at 12 months was 29% (95% CI: 16%, 42%). Median progression-free survival was 4.4 months. Overall survival at 6 months was 74% (95% CI: 62%, 86%) and 12-month overall survival was 65% (95% CI: 52%, 78%). Median overall survival was 15.9 months.

15. REFERENCES

1. "OSHA Hazardous Drugs." OSHA. http://www.osha.gov/SLTC/hazardousdrugs/index.

16. HOW SUPPLIED/STORAGE AND HANDLING

TEMOZOLOMIDE is a cytotoxic drug. Follow applicable special handling and disposal procedures.

TEMOZOLOMIDE Capsules, USP are supplied in amber glass bottles, with child-resistant polypropylene caps (not supplied in sachets) containing the following capsule strengths:

TEMOZOLOMIDE Capsules USP, 5 mg: | Have opaque white bodies with opaque green caps. The capsule body is imprinted with the dosage strength. They are supplied as follows: Bottles: 5-count – NDC 67877-537-07 14-count – NDC 67877-537-14
TEMOZOLOMIDE Capsules USP, 20 mg: | Have opaque white bodies with opaque yellow caps. The capsule body is imprinted with the dosage strength. They are supplied as follows: Bottles: 5-count – NDC 67877-538-07 14-count – NDC 67877-538-14
TEMOZOLOMIDE Capsules USP, 100 mg: | Have opaque white bodies with opaque flesh caps. The capsule body is imprinted with the dosage strength. They are supplied as follows: Bottles: 5-count – NDC 67877-539-07 14-count – NDC 67877-539-14
TEMOZOLOMIDE Capsules USP, 140 mg: | Have opaque white bodies with transparent blue caps. The capsule body is imprinted with the dosage strength. They are supplied as follows: Bottles: 5-count – NDC 67877-540-07 14-count – NDC 67877-540-14
TEMOZOLOMIDE Capsules USP, 180 mg: | Have opaque white bodies with opaque orange caps. The capsule body is imprinted with the dosage strength. They are supplied as follows: Bottles: 5-count – NDC 67877-541-07 14-count – NDC 67877-541-14
TEMOZOLOMIDE Capsules USP, 250 mg: | Have opaque white bodies with opaque white caps. The capsule body is imprinted with the dosage strength. They are supplied as follows: Bottles: 5-count – NDC 67877-542-07

Store TEMOZOLOMIDE Capsules at 25°C (77°F); excursions permitted to 15°C to 30°C (59°F to 86°F) [see USP Controlled Room Temperature].

17. PATIENT COUNSELING INFORMATION

Advise the patient to read the FDA-approved patient labeling (Patient Information).

Myelosuppression

Inform patients that TEMOZOLOMIDE can cause low blood cell counts and the need for frequent monitoring of blood cell counts. Advise patients to contact their healthcare provider immediately for bleeding, fever, or other signs of infection [see Warnings and Precautions (5.1)].

Myelodysplastic Syndrome and Secondary Malignancies

Advise patients of the increased risk of myelodysplastic syndrome and secondary malignancies [see Warnings and Precautions (5.2)].

Pneumocystis Pneumonia

Advise patients of the increased risk of Pneumocystis pneumonia and to contact their healthcare provided immediately for new or worsening pulmonary symptoms. Inform patients that prophylaxis for Pneumocystis pneumonia may be needed [see Dosage and Administration (2.1), Warnings and Precautions (5.3)].

Hepatotoxicity

Advise patients of the increased risk of hepatotoxicity and to contact their healthcare provider immediately for signs or symptoms of hepatoxicity [see Warnings and Precautions (5.4)].

Administration Instructions

Advise patient to not open capsules. If capsules are accidentally opened or damaged, advise patients to take rigorous precautions with capsule contents to avoid inhalation or contact with the skin or mucous membranes. In case of powder contact, the hands should be washed. [see Dosage and Administration (2.3)].

Embryo-Fetal Toxicity

Advise pregnant women and females of reproductive potential of the potential risk to a fetus. Advise females to inform their healthcare provider of a known or suspected pregnancy [see Warnings and Precautions (5.5), Use in Specific Populations (8.1)].

Advise females of reproductive potential to use effective contraception during treatment with TEMOZOLOMIDE and for at least 6 months after the last dose [see Use in Specific Populations (8.3)].

Advise male patients with pregnant partners or female partners of reproductive potential to use condoms during treatment with TEMOZOLOMIDE and for at least 3 months after the final dose [see Use in Specific Populations (8.3), Nonclinical Toxicology (13.1)].

Advise male patients not to donate semen during treatment with TEMOZOLOMIDE and for at least 3 months after the final dose [see Use in Specific Populations (8.3), Nonclinical Toxicology (13.1)].

Lactation

Advise women not to breastfeed during treatment with TEMOZOLOMIDE and for at least 1 week after the final dose [see Use in Specific Populations (8.2)].

Infertility

Advise males of reproductive potential that TEMOZOLOMIDE may impair fertility [see Use in Specific Populations (8.3), Nonclinical Toxicology (13.1)].

Manufactured by:

Deva Holding A.S.

Distributed by:

Ascend Laboratories, LLC

339 Jefferson Road

Parsippany, NJ 07054

Revised: 02/2023

Patient Information

TEMOZOLOMIDE (TEM-oh-ZOL-oh-mide) Capsules, USP
What is the most important information I should know about TEMOZOLOMIDE?
TEMOZOLOMIDE may cause birth defects.
Females and female partners of male patients who take TEMOZOLOMIDE:
o Avoid becoming pregnant while taking TEMOZOLOMIDE.
o Females who can become pregnant should use an effective form of birth control (contraception) during treatment and for at least 6 months after your last dose of TEMOZOLOMIDE. Your doctor should to do a pregnancy test to make sure that you are not pregnant before you start taking TEMOZOLOMIDE.
o Tell your doctor right away if you become pregnant or think you are pregnant during treatment with TEMOZOLOMIDE.
Males taking TEMOZOLOMIDE and have a female partner who is pregnant or who can become pregnant:
o Use a condom for birth control (contraception) during treatment and for at least 3 months after taking your final dose of TEMOZOLOMIDE.
o Do not donate semen during treatment and for at least 3 months after your final dose of TEMOZOLOMIDE.
See the section "What are the possible side effects of TEMOZOLOMIDE?" for more information about side effects.
What is TEMOZOLOMIDE?
TEMOZOLOMIDE is a prescription medicine used to treat adults with certain brain cancer tumors. It is not known if TEMOZOLOMIDE is safe and effective in children.
Who should not take TEMOZOLOMIDE?
Do not take TEMOZOLOMIDE if you:
• have had an allergic reaction to temozolomide or any of the other ingredients in TEMOZOLOMIDE. See the end of this leaflet for a list of ingredients in TEMOZOLOMIDE. Symptoms of an allergic reaction with TEMOZOLOMIDE may include: a red itchy rash, or a severe allergic reaction, such as trouble breathing, swelling of the face, throat, or tongue, or severe skin reaction. If you are not sure, ask your doctor.
• have had an allergic reaction to dacarbazine (DTIC), another cancer medicine.
What should I tell my doctor before taking TEMOZOLOMIDE?
Tell your doctor about all your medical conditions, including if you:
• have kidney problems
• have liver problems
• are pregnant or plan to become pregnant. See “What is the most important information I should know about TEMOZOLOMIDE?”
• are breast-feeding or plan to breastfeed. It is not known if TEMOZOLOMIDE passes into your breast milk. Do not breastfeed during treatment and for at least 1 week after your last dose of TEMOZOLOMIDE.
Tell your doctor about all the medicines you take, including prescription and non-prescription medicines, vitamins, and herbal supplements. Especially tell your doctor if you take a medicine that contains valproic acid.
Know the medicines you take. Keep a list of them and show it to your doctor and pharmacist when you get a new medicine.
How should I take TEMOZOLOMIDE?
TEMOZOLOMIDE may be taken 2 different ways:
o you may take TEMOZOLOMIDE by mouth as a capsule, or
o you may receive TEMOZOLOMIDE as an intravenous (IV) injection into your vein. Your doctor will decide the best way for you to take TEMOZOLOMIDE. Take TEMOZOLOMIDE exactly as prescribed by your doctor.
There are 2 common dosing schedules for taking TEMOZOLOMIDE depending on the type of brain cancer tumor that you have.
•People with certain brain can cancer tumors take or receive TEMOZOLOMIDE:
o 1 time each day for 42 days in a row (possibly 49 days depending on side effects) along with receiving radiation treatment. This is 1 cycle of treatment.
o After this, your doctor may prescribe 6 more cycles of TEMOZOLOMIDE as “maintenance” treatment. For each of these cycles, you take or receive TEMOZOLOMIDE 1 time each day for 5 days in a row and then you stop taking it for the next 23 days. This is a 28-day maintenance treatment cycle.
•People with certain other brain cancer tumors take or receive TEMOZOLOMIDE:
o 1 time each day for 5 days in a row only, and then stop taking it for the next 23 days. This is 1 cycle of treatment (28 days).
o Your doctor will watch your progress on TEMOZOLOMIDE and decide how long you should take it. You might take TEMOZOLOMIDE until your tumor gets worse or for possibly up to 2 years.
•If your doctor prescribes a treatment regimen that is different from the information in this leaflet, make sure you follow the instructions given to you by your doctor.
•Your doctor may change your dose of TEMOZOLOMIDE, or tell you to stop TEMOZOLOMIDE for a short period of time or permanently if you have certain side effects.
•Your doctor will decide how many treatment cycles of TEMOZOLOMIDE that you will receive, depending on how you respond to and tolerate treatment.
TEMOZOLOMIDE Capsules, USP:
•Take TEMOZOLOMIDE Capsules, USP exactly as your doctor tells you to.
•TEMOZOLOMIDE capsules contain a white capsule body with a color cap and the colors vary based on the dosage strength. Your doctor may prescribe more than 1 strength of TEMOZOLOMIDE capsules, USP for you, so it is important that you understand how to take your medicine the right way. Be sure that you understand exactly how many capsules you need to take on each day of your treatment, and what strengths to take. This may be different whenever you start a new cycle.
•Do not take more TEMOZOLOMIDE than prescribed.
•Talk to your doctor or pharmacist before taking your dose if you are not sure how much TEMOZOLOMIDE to take. This will help to prevent taking too much TEMOZOLOMIDE and decrease your chances of getting serious side effects.
•Take each day’s dose of TEMOZOLOMIDE Capsules, USP at one time, with a full glass of water.
•Swallow TEMOZOLOMIDE Capsules, USP whole. Do not chew, open, or split the capsules.
•Take TEMOZOLOMIDE capsules, USP at the same time each day.
•Take TEMOZOLOMIDE the same way each time, either with food or without food.
•If TEMOZOLOMIDE Capsules, USP are accidentally opened or damaged, be careful not to breathe in (inhale) the powder from the capsules or get the powder on your skin or mucous membranes (for example, in your nose or mouth). If contact with any of these areas happens, flush the area with water.
•To help reduce nausea and vomiting, try to take TEMOZOLOMIDE on an empty stomach or at bedtime. Your doctor may prescribe medicine to help prevent or treat nausea, or other medicines to reduce side effects with TEMOZOLOMIDE .
•See your doctor regularly to check your progress. Your doctor will check you for side effects.
•If you take more TEMOZOLOMIDE than prescribed, call your doctor or get emergency medical help right away.
What are the possible side effects of TEMOZOLOMIDE?
TEMOZOLOMIDE can cause serious side effects, including:
•See “What is the most important information I should know about TEMOZOLOMIDE?”
•Decreased blood cell counts.
TEMOZOLOMIDE can affect your bone marrow and cause you to have decreased blood cell counts. Decreased white blood cell count, red blood cell count and platelet count are common with TEMOZOLOMIDE but it can also be severe and lead to death.
o Your doctor will do blood tests regularly to check your blood cell counts before you start and during treatment with TEMOZOLOMIDE.
o Your doctor may need to change the dose of TEMOZOLOMIDE, or when you get it depending on your blood cell counts.
o People who are age 70 or older and women have a higher risk for developing decreased blood cell counts during treatment with TEMOZOLOMIDE.
•Secondary cancers. Blood problems such as myelodysplastic syndrome (MDS) and new cancers (secondary cancers), including a certain kind of leukemia, can happen in people who take TEMOZOLOMIDE. Your doctor will monitor you for this.
•Pneumocystis pneumonia (PCP). PCP is an infection that people can get when their immune system is weak. TEMOZOLOMIDE decreases white blood cells, which makes your immune system weaker and can increase your risk of getting PCP.
o People who are taking steroid medicines or who stay on TEMOZOLOMIDE for a longer period of time may have an increased risk of getting PCP infection.
o Anyone who takes TEMOZOLOMIDE will be watched carefully by their doctor for low blood cell counts and this infection.
o Tell your doctor if you have any of the following signs and symptoms of PCP infection: shortness of breath, or fever, chills, dry cough.
•Liver problems. Liver problems can happen with TEMOZOLOMIDE and can sometimes be severe and lead to death. Your doctor will do blood tests to check your liver function before you start taking TEMOZOLOMIDE , during treatment, and about 2 to 4 weeks after your last dose of TEMOZOLOMIDE .
Common side effects with TEMOZOLOMIDE include:
•hair loss
•feeling tired
•nausea and vomiting.
•headache
•constipation
•loss of appetite
•convulsions
•rash
•diarrhea
•unable to move (paralysis) on one side of the body
•weakness
•fever
•dizziness
•coordination problems
•viral infection
•memory loss
•sleep problems
TEMOZOLOMIDE can affect fertility in males and may affect your ability to father a child. Talk with your doctor if fertility is a concern for you.
Tell your doctor about any side effect that bothers you or that does not go away.
These are not all the possible side effects with TEMOZOLOMIDE. For more information, ask your doctor or pharmacist.
Call your doctor for medical advice about side effects. You may report side effects to FDA at 1-800-FDA-1088.
How should I store TEMOZOLOMIDE Capsules, USP?
• Store TEMOZOLOMIDE Capsules, USP at 77°F (controlled room temperature). Storage at 59°F to 86°F (15°C to 30°C) is permitted occasionally.
• Keep TEMOZOLOMIDE Capsules, USP out of the reach of children.
General information about the safe and effective use of TEMOZOLOMIDE.
Medicines are sometimes prescribed for purposes other than those listed in the Patient Information leaflet. Do not use TEMOZOLOMIDE for a condition for which it was not prescribed. Do not give TEMOZOLOMIDE to other people, even if they have the same symptoms that you have. It may harm them.
This leaflet summarizes the most important information about TEMOZOLOMIDE. If you would like more information, talk with your doctor. You can ask your pharmacist or doctor for information about TEMOZOLOMIDE that is written for health professionals.
For more information, contact Ascend Laboratories, LLC at 1-877-ASC-RX01 (877-272-7901).
What are the ingredients in TEMOZOLOMIDE?
TEMOZOLOMIDE Capsules, USP:
Active ingredient: temozolomide.
Inactive ingredients: lactose anhydrous, sodium starch glycolate, colloidal silicon dioxide, tartaric acid, and stearic acid.
The body of the capsules is made of gelatin and titanium dioxide and is opaque white. The cap is also made of gelatin and the colors vary based on the dosage strength. The capsule body and cap are imprinted with pharmaceutical branding ink, which contains shellac, iron oxide black, n-butyl alcohol, purified water, propylene glycol, dehydrated ethanol, isopropyl alcohol and ammonium hydroxide.
TEMOZOLOMIDE 5 mg: The opaque green cap contains gelatin, titanium dioxide, iron oxide yellow and FD&C Blue #2.
TEMOZOLOMIDE 20 mg: The opaque yellow cap contains gelatin, titanium dioxide and iron oxide yellow.
TEMOZOLOMIDE 100 mg: The opaque flesh cap contains gelatin, titanium dioxide and iron oxide red.
TEMOZOLOMIDE 140 mg: The transparent blue cap contains gelatin and FD&C Blue #2
TEMOZOLOMIDE 180 mg: The opaque orange cap contains gelatin, titanium dioxide and iron oxide red.
TEMOZOLOMIDE 250 mg: The opaque white cap contains gelatin and titanium dioxide.
Manufactured by:
Deva Holding A.S.

Distributed by:
Ascend Laboratories, LLC
339 Jefferson Road
Parsippany, NJ 07054

Revised: 02/2023

TEMOZOLOMIDE Capsules, USP
PHARMACIST:
Dispense enclosed Patient Package Insert to each patient.
PHARMACIST INFORMATION SHEET

IMPORTANT DISPENSING INFORMATION
For every patient, TEMOZOLOMIDE must be dispensed in a separate vial or in its original package, making sure each container lists the strength per capsule and that patients take the appropriate number of capsules from each package or vial. Please see the dispensing instructions below for more information.

What is TEMOZOLOMIDE?[See Full Prescribing Information, Indications and Usage (1).]
TEMOZOLOMIDE is an oral alkylating agent for the treatment of newly diagnosed glioblastoma multiforme and refractory anaplastic astrocytoma.

How is TEMOZOLOMIDE dosed?
[See Full Prescribing Information, Recommended Dosage and Dosage Modifications for Newly Diagnosed Glioblastoma (2.1), Recommended Dosage and Dosage Modifications for Refractory Anaplastic Astrocytoma (2.2).]

The physician calculates the daily dose of TEMOZOLOMIDE capsules for a given patient based on the patient’s body surface area (BSA). Round off the resulting dose to the nearest 5 mg. An example of the dosing may be as follows: the initial daily dose of TEMOZOLOMIDE in milligrams is the BSA multiplied by mg/m2/day (e.g., a patient with a BSA of 1.84 is 1.84 x 75 mg = 138, or 140 mg/day). Adjust the dose for subsequent cycles according to nadir neutrophil and platelet counts in the previous cycle and at the time of initiating the next cycle.

How might the dose of TEMOZOLOMIDE be modified for Refractory Anaplastic Astrocytoma?[See Full Prescribing Information, Recommended Dosage and Dosage Modifications for Refractory Anaplastic Astrocytoma (2.2).]

The initial dose is 150 mg/m2 orally once daily for 5 consecutive days per 28-day treatment cycle. Increase the TEMOZOLOMIDE dose to 200 mg/m2/day for 5 consecutive days per 28-day treatment cycle if both the nadir and day of dosing (Day 29, Day 1 of next cycle) absolute neutrophil counts (ANC) are greater than or equal to 1.5 x 109/L (1500/μL) and both the nadir and Day 29, Day 1 of next cycle platelet counts are greater than or equal to 100 x 109/L (100,000/μL). During treatment, obtain a complete blood count on Day 22 (21 days after the first dose), and weekly until the ANC is above 1.5 x 109/L (1500/μL) and the platelet count exceeds 100 x 109/L (100,000/μL). Do not start the next cycle of TEMOZOLOMIDE until the ANC and platelet count exceed these levels. If the ANC falls to less than 1.0 x 109/L (1000/μL) or the platelet count is less than 50 x 109/L (50,000/μL) during any cycle, reduce the dose for the next cycle by 50 mg/m2. Permanently discontinue TEMOZOLOMIDE in patients who are unable to tolerate a dose of 100 mg/m2 per day.

Patients should continue taking TEMOZOLOMIDE until their physician determines that their disease has progressed or until unacceptable side effects or toxicities occur. In the clinical trial, treatment could be continued for a maximum of 2 years, but the optimum duration of therapy is not known. Physicians may alter the treatment regimen for a given patient.

Dosing for Patients with Newly Diagnosed Glioblastoma Multiforme [See Full Prescribing Information, Recommended Dosage and Dosage Modifications for Newly Diagnosed Glioblastoma (2.1).]

Concomitant Phase Treatment Schedule
Administer TEMOZOLOMIDE orally at 75 mg/m2 daily for 42 days concomitant with focal radiotherapy (60 Gy administered in 30 fractions), followed by maintenance TEMOZOLOMIDE for 6 cycles. No dose reductions are recommended; however, dose interruptions may occur based on patient tolerance. Continue the TEMOZOLOMIDE dose throughout the 42-day concomitant period up to 49 days if all of the following conditions are met: absolute neutrophil count greater than or equal to 1.5 x 109/L, platelet count greater than or equal to 100 x109/L, and nonhematological adverse reactions less than or equal to Grade 1 (except for alopecia, nausea and vomiting). During treatment, obtain a complete blood count weekly. Interrupt or discontinue temozolomide dosing during the concomitant phase according to the hematological and nonhematological toxicity criteria [see Table 1 in the Full Prescribing Information, Recommended Dosage and Dosage Modifications for Newly Diagnosed Glioblastoma (2.1)]. Pneumocystis pneumonia (PCP) prophylaxis is required during the concomitant administration of TEMOZOLOMIDE and radiotherapy, and should be continued in patients who develop lymphocytopenia until resolution to Grade 1 or less.

Maintenance Phase Treatment Schedule
Four weeks after completing the TEMOZOLOMIDE and radiotherapy phase, administer TEMOZOLOMIDE for an additional 6 cycles of maintenance treatment. Dosage in Cycle 1 (maintenance) is 150 mg/m2 once daily for 5 days followed by 23 days without treatment. At the start of Cycle 2, escalate the dose to 200 mg/m2, if the nonhematologic adverse reactions for Cycle 1 are Grade less than or equal to 2 (except for alopecia, nausea and vomiting), absolute neutrophil count (ANC) is greater than or equal to 1.5 x 109/L, and the platelet count is greater than or equal to 100 x 109/L. If the dose was not escalated at Cycle 2, do not escalate the dose in subsequent cycles. Maintain the dose at 200 mg/m2 per day for the first 5 days of each subsequent cycle except if toxicity occurs.

During treatment, obtain a complete blood count on Day 22 (21 days after the first dose) and weekly until the ANC is above 1.5 x 109/L (1500/μL) and the platelet count exceeds 100 x 109/L (100,000/μL). Do not start the next cycle of TEMOZOLOMIDE until the ANC and platelet count exceed these levels. Base dose reductions during the next cycle on the lowest blood counts and worst nonhematologic adverse reactions during the previous cycle. Apply dose reductions or discontinuations during the maintenance phase [see Table 2 in the Full Prescribing Information, Recommended Dosage and Dosage Modifications for Newly Diagnosed Glioblastoma (2.1)].

How is TEMOZOLOMIDE taken?[See Full Prescribing Information, Preparation and Administration, TEMOZOLOMIDE capsules (2.3).]
Advise patients to take each day’s dose with a full glass of water, preferably on an empty stomach or at bedtime. Taking the medication on an empty stomach or at bedtime may help ease nausea. If patients are also taking anti-nausea or other medications to relieve the side effects associated with TEMOZOLOMIDE, advise them to take these medications prior to and/or following administration of TEMOZOLOMIDE capsules. Advise patients that TEMOZOLOMIDE capsules should be swallowed whole and NEVER CHEWED. Advise patients that they SHOULD NOT open or split the capsules. If capsules are accidentally opened or damaged, advise patients to take rigorous precautions with the capsule contents to avoid inhalation or contact with the skin or mucous membranes. In case of powder contact, advise the patients to wash their hands. Advise patients to keep this medication away from children.

What should the patient avoid during treatment with TEMOZOLOMIDE?[See Full Prescribing Information, Use in Specific Populations, Pregnancy (8.1), Lactation (8.2), Females and Males of Reproductive Potential (8.3).]

There are no dietary restrictions for patients taking TEMOZOLOMIDE. TEMOZOLOMIDE may affect testicular function and may cause birth defects. Advise male patients to exercise adequate birth control measures. Advise female patients to avoid becoming pregnant while receiving this drug. Advise pregnant women of the potential risk to the fetus. Advise females of reproductive potential to use effective contraception during treatment and for at least 6 months after the last dose. Advise males of reproductive potential to use condoms during treatment and for at least 3 months after the last dose. Advise male patients not to donate semen during treatment with TEMOZOLOMIDE and for at least 3 months after the final dose. It is not known whether TEMOZOLOMIDE is excreted into breast milk. Because of the potential for serious adverse reactions in breastfed children, advise women not to breastfeed while taking TEMOZOLOMIDE and for at least 1 week after the last dose.

What are the side effects of TEMOZOLOMIDE?[See Full Prescribing Information, Adverse Reactions (6).]
Alopecia, fatigue, nausea, and vomiting are the most common side effects associated with TEMOZOLOMIDE. Noncumulative myelosuppression is the dose-limiting toxicity. Patients should be evaluated periodically by their physician to monitor blood counts.
Other commonly reported side effects reported by patients taking TEMOZOLOMIDE are headache, constipation, anorexia, and convulsions.

How is TEMOZOLOMIDE supplied?[See Full Prescribing Information, How Supplied/Storage and Handling(16).]

TEMOZOLOMIDE Capsules, USP are available in 5-mg, 20-mg, 100-mg, 140-mg, 180-mg, and 250-mg strengths. The capsules contain a opaque white capsule body with a color cap, and the colors vary based on the dosage strength.

TEMOZOLOMIDE Capsule, USP
Strength Color
5 mg Opaque Green Cap
20 mg Opaque Yellow Cap
100 mg Opaque Flesh Cap
140 mg Transparent Blue Cap
180 mg Opaque Orange Cap
250 mg Opaque White Cap
The 5 mg, 20 mg, 100 mg, 140 mg, and 180 mg capsule strengths are available in 5 count and 14 count packages. The 250 mg capsule strength is available in a 5 count package.

How is TEMOZOLOMIDE dispensed?
Dispense each strength of TEMOZOLOMIDE in a separate vial or in its original package (one strength per one container). Follow the instructions below: Based on the dose prescribed, determine the number of each strength of TEMOZOLOMIDE capsules needed for the full 42-or 5-day cycle as prescribed by the physician. For example, in a 5-day cycle, 275 mg/day would be dispensed as five 250-mg capsules, five 20-mg capsules and five 5-mg capsules. Label each container with the appropriate number of capsules to be taken each day. Dispense to the patient, making sure each container lists the strength (mg) per capsule and that he or she understands to take the appropriate number of capsules of TEMOZOLOMIDE from each package or vial to equal the total daily dose prescribed by the physician.

How can TEMOZOLOMIDE be ordered?
TEMOZOLOMIDE can be ordered from your wholesaler. It is important to understand if TEMOZOLOMIDE is being used as part of a 42 day regimen or as part of a 5 day course. Remember to order enough TEMOZOLOMIDE for the appropriate cycle.

For example:

• a 5 day course of 360 mg/day would require the following to be ordered: two 5 count packages of 180 mg capsules.
• a 42 day course of 140 mg/day would require the following to be ordered: three 14 count packages of 140 mg capsules.

Temozolomide Bottles Product NDC Number
5-mg capsules (5 count) 67877-537-07
5-mg capsules (14 count) 67877-537-14

20-mg capsules (5 count) 67877-538-07

20-mg capsules (14 count) 67877-538-14

100-mg capsules (5 count) 67877-539-07

100-mg capsules (14 count) 67877-539-14

140-mg capsules (5 count) 67877-540-07

140-mg capsules (14 count) 67877-540-14

180-mg capsules (5 count) 67877-541-07

180-mg capsules (14 count) 67877-541-14

250-mg capsules (5 count) 67877-542-07

Manufactured by:
Deva Holding A.S.

Distributed by:
Ascend Laboratories, LLC
339 Jefferson Road
Parsippany, NJ 07054

Revised:02/2023

CKY1632KT-11

PACKAGE LABEL PRINCIPAL DISPLAY PANEL

NDC 67877-537-07
For Oral Administration
Rx only

NDC 67877-538-07
For Oral Administration
Rx only

NDC 67877-539-07
For Oral Administration
Rx only

NDC 67877-540-07
For Oral Administration
Rx only

NDC 67877-541-07
For Oral Administration
Rx only

NDC 67877-542-07
For Oral Administration
Rx only